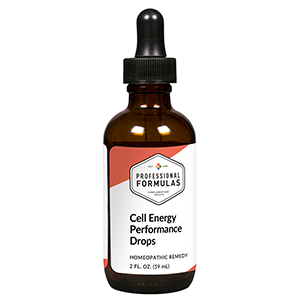 DRUG LABEL: Cell Energy Performance Drops
NDC: 63083-2048 | Form: LIQUID
Manufacturer: Professional Complementary Health Formulas
Category: homeopathic | Type: HUMAN OTC DRUG LABEL
Date: 20190815

ACTIVE INGREDIENTS: VITIS VINIFERA SEED 6 [hp_X]/59 mL; ANHYDROUS CITRIC ACID 8 [hp_X]/59 mL; COENZYME A 8 [hp_X]/59 mL; NADH 8 [hp_X]/59 mL; PHOSPHORUS 9 [hp_X]/59 mL; CALCIUM PYRUVATE 12 [hp_X]/59 mL; GERMANIUM 12 [hp_X]/59 mL; ANHYDROUS DEXTROSE 12 [hp_X]/59 mL; CARNITINE 30 [hp_X]/59 mL; UBIDECARENONE 30 [hp_X]/59 mL; IRON 30 [hp_X]/59 mL; LACTIC ACID, DL- 30 [hp_X]/59 mL; RIBOFLAVIN 30 [hp_X]/59 mL; ALPHA LIPOIC ACID 30 [hp_X]/59 mL; ADENOSINE TRIPHOSPHATE 30 [hp_X]/59 mL; CARBON DIOXIDE 200 [hp_X]/59 mL; DALOTUZUMAB 200 [hp_X]/59 mL
INACTIVE INGREDIENTS: ALCOHOL; WATER

C48

ACTIVE INGREDIENTS

Grape seed 6X
Kreb's cycle 8X
Coenzyme A 8X, 12X, 30X
NADH 8X, 30X, 100X, 200X
Phosphorus 9X
Calcium pyruvate 12X
Germanium 12X
Glucose 12X
Carnitine 30X
Coenzyme Q10 30X
Iron 30X
Lacticum acidum 30X
Riboflavin 30X
Alpha-Lipoicum acidum 30X, 100X, 200X
ATP 30X, 100X, 200X
Carbon dioxide 200X
IGF-1 200X

QUESTIONS

Professional Formulas

PO Box 2034 Lake Oswego, OR 97035

INDICATIONS

For the temporary relief of exhaustion, muscle weakness, lethargy, or tiring easily.*

PURPOSE

*Claims based on traditional homeopathic practice, not accepted medical evidence. Not FDA evaluated.

WARNINGS

In case of overdose, get medical help or contact a poison control center right away.

Keep out of the reach of children.

PREGNANCY OR BREAST FEEDING

If pregnant or breastfeeding, ask a healthcare professional before use.

DIRECTIONS

Place drops under tongue 30 minutes before/after meals. Adults and children 12 years and over: Take 10 drops up to 3 times per day. Consult a physician for use in children under 12 years of age.

OTHER INFORMATION

Tamper resistant. If seal is broken, do not use. After opening, close container tightly and store at room temperature away from heat.

INACTIVE INGREDIENTS

20% ethanol, purified water.

LABEL

Est 1985

Professional Formulas

Complementary Health

Cell Energy Performance Drops

Homeopathic Remedy

2 FL. OZ. (59 mL)